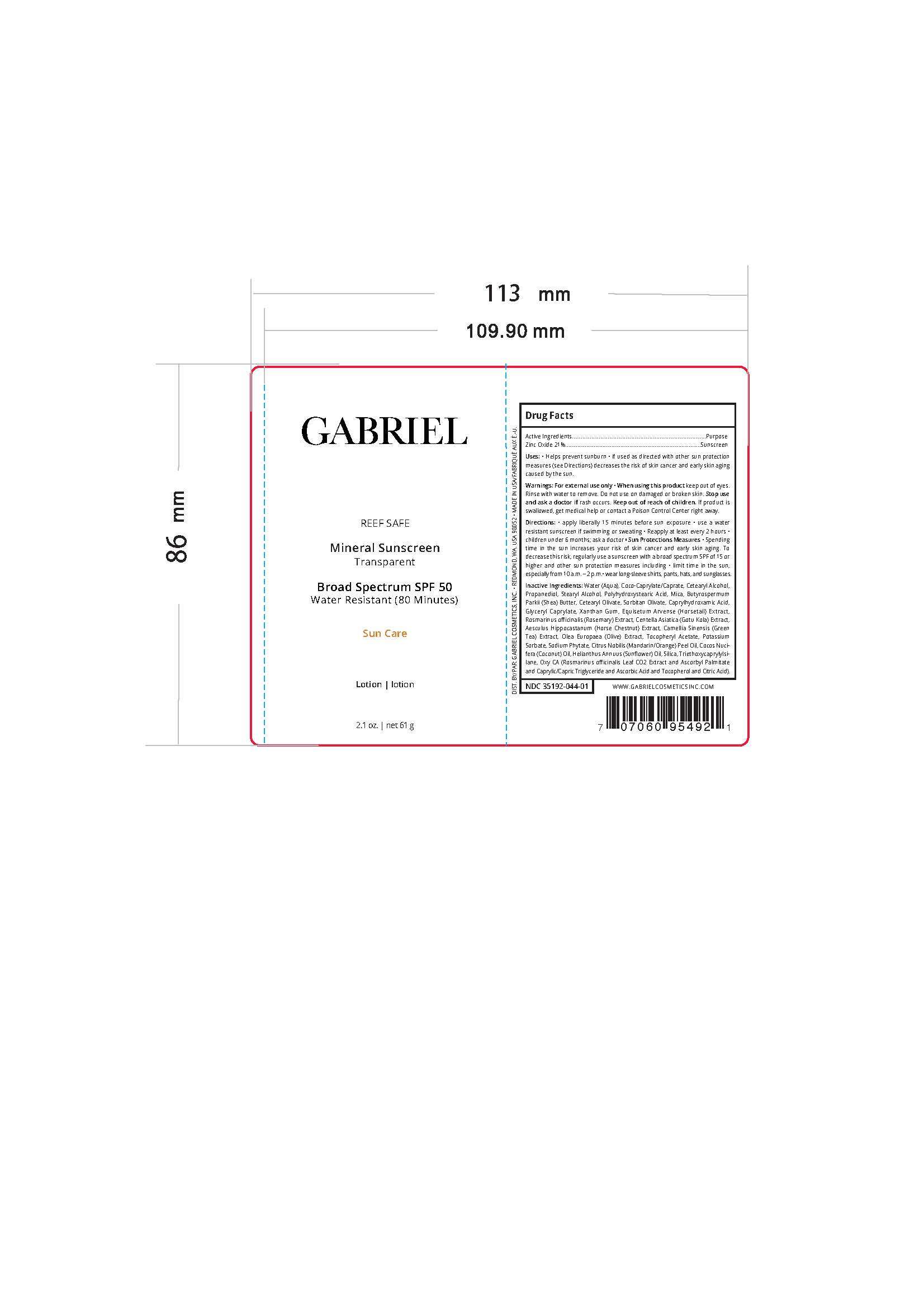 DRUG LABEL: Mineral Sunscreen
NDC: 35192-044 | Form: EMULSION
Manufacturer: CA-Botana International
Category: otc | Type: HUMAN OTC DRUG LABEL
Date: 20251216

ACTIVE INGREDIENTS: ZINC OXIDE 12.81 g/12.81 g
INACTIVE INGREDIENTS: TOCOPHEROL; XANTHAN GUM; GLYCERIN; PROPANEDIOL; WATER; ANHYDROUS CITRIC ACID; COCO-CAPRYLATE/CAPRATE; CAPRYLHYDROXAMIC ACID; SORBITAN OLIVATE; EQUISETUM ARVENSE WHOLE; ASCORBIC ACID; SUNFLOWER OIL; DIMETHICONOL TRIETHOXYCAPRYLYLSILANE TETRAETHYL SILICATE CROSSPOLYMER (4000000 MW); STEARYL ALCOHOL; POLYHYDROXYSTEARIC ACID (2300 MW); CETEARYL OLIVATE; ALLANTOIN; ROSEMARY; HEXASODIUM PHYTATE; POTASSIUM SORBATE; ETHYL FERULATE; GLYCERYL CAPRATE; CENTELLA ASIATICA; GREEN OLIVE; .ALPHA.-TOCOPHEROL ACETATE, DL-; ORANGE PEEL; COCOS NUCIFERA WHOLE; HYDRATED SILICA; ASCORBYL PALMITATE; MICA; CETOSTEARYL ALCOHOL; MEDIUM-CHAIN TRIGLYCERIDES; HORSE CHESTNUT; GREEN TEA LEAF; SHEA BUTTER

DS Mineral Sunscreen SPF 50 Gabriel

Active Ingredient

Zinc Oxide 21%............................................. Sunscreen

Purpose

Sunscreen

Ask Doctor

Stop use and ask a doctor if rash occurs

Keep out of reach of children

Inactive Ingredients

Water (Aqua), Coco-Caprylate/Caprate, Ceteary Alcohol, Propanediol, Stearyl Alcohol, Polyhydroxystearic Acid, Mica, Butyrospermun parki (Shea butter), Cetearyl Olivate, Sorbitan Olivate, Caaprylhydroxamic acid. GlycerylCaprylate, Glycerin, Xanthan Gum, Equisetum arvense (Horsetail) extract, Rosmarinus officinalis (Rosemary) extract, Centella asiatica(Gotu-kola) extract, Aesculus hippocastanum (Horse chestnut) extract, Camellia sinensis(Green tea) extract, Olea europaea (Olive) extract, Tocopheryl Acetate, Potassium Acetate, Sodium Phytate, Citrus nobilis/Mandarinorage) Peel oil, Coconut oil, Helianthus annuus (Sunflower) Seed oil, Silica, Triethpxycapryylsilane, OXY CA (Rosmarinus officnalis (Leaf)CO2 Extract& Ascorbyl Palmitate & Caprylic/Capric Triglyceride & Ascorbic Acid & Tocopherol & Citric Acid)

Safety information

Protect this product from excessive heat and direct sun

Dosage & Administration

Helps prevent sunburn. If used as directed with other sun protection measured decreases the risk of skin cancer and early skin aging caused by the sun. Apply liberally 15 minutes before sun exposure. Usea water resistant sunscreen if swimming or sweating. Reapply : at least 2 hours. Children under 6 months: Ask a doctor. Sun protections measurements. Spending time in the sun increases your risk of skin cancer and early skin aging. To decrease this risk, regularly use a sunscreen with a broad spectrum SPF of 15 or higher and othe sun protection measures including: limit time in the sun, specially from 10 a.m.- 2 p.m Wear long-sleeveshirts, pants, hats, and sunglasses. Protect this product from excessive heat and direct sun.

Warnings

For external use only. Do not use on damaged or broken skin. When using this product keep out of eyes. Rinse with water to remove. If product is swallowed get medical help or contact a poison Control Center right away.

Indications & Usage

Apply liberally 15 minutes before exposure, use water resistant sunscreen, if swimming or sweating. reapply at least every 2 hours. Children under 6 months: ask a doctor